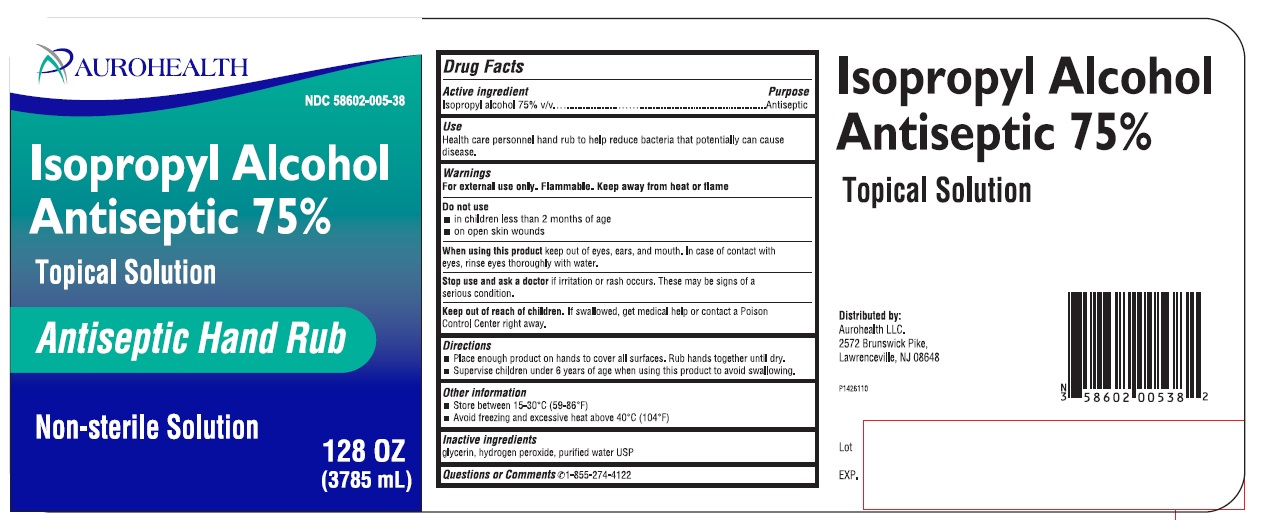 DRUG LABEL: Isopropyl Alcohol Antiseptic 75%
NDC: 58602-005 | Form: SOLUTION
Manufacturer: Aurohealth LLC
Category: otc | Type: Human OTC Drug Label
Date: 20200625

ACTIVE INGREDIENTS: ISOPROPYL ALCOHOL 75 mL/100 mL
INACTIVE INGREDIENTS: GLYCERIN; HYDROGEN PEROXIDE; WATER

Isopropyl Alcohol Antiseptic 75% Topical Solution
Antiseptic Hand Rub

ACTIVE INGREDIENT(S)

Isopropyl alcohol 75% v/v

PURPOSE

Antiseptic

USE(S)

Health care personnel hand rub to help reduce bacteria that potentially can cause disease.

WARNINGS

For external use only. Flammable. Keep away from heat or flame

DO NOT USE

- in children less than 2 months of age
- on open skin wounds

When using this product keep out of eyes, ears, and mouth. In case of contact with eyes, rinse eyes thoroughly with water.

STOP USE AND ASK DOCTOR IF

Stop use and ask a doctor if irritation or rash occurs. These may be signs of a serious condition.

Keep out of reach of children. If swallowed, get medical help or contact a Poison Control Center right away.

DIRECTIONS

- Place enough product on hands to cover all surfaces. Rub hands together until dry.
- Supervise children under 6 years of age when using this product to avoid swallowing.

OTHER INFORMATION

- Store between 15-30^0C (59-86^0F)
- Avoid freezing and excessive heat about 40^0C (104^0F)

INACTIVE INGREDIENT SECTION

Glycerin, hydrogen peroxide, purified water USP

QUESTIONS OR COMMENTS

1-855-274-422

PRINCIPAL DISPLAY PANEL

NDC 58602-005-38
Isopropyl Alcohol Antiseptic 75%
Topical Solution
Antiseptic Hand Rub
Non-sterile Solution
128 OZ (3785mL)